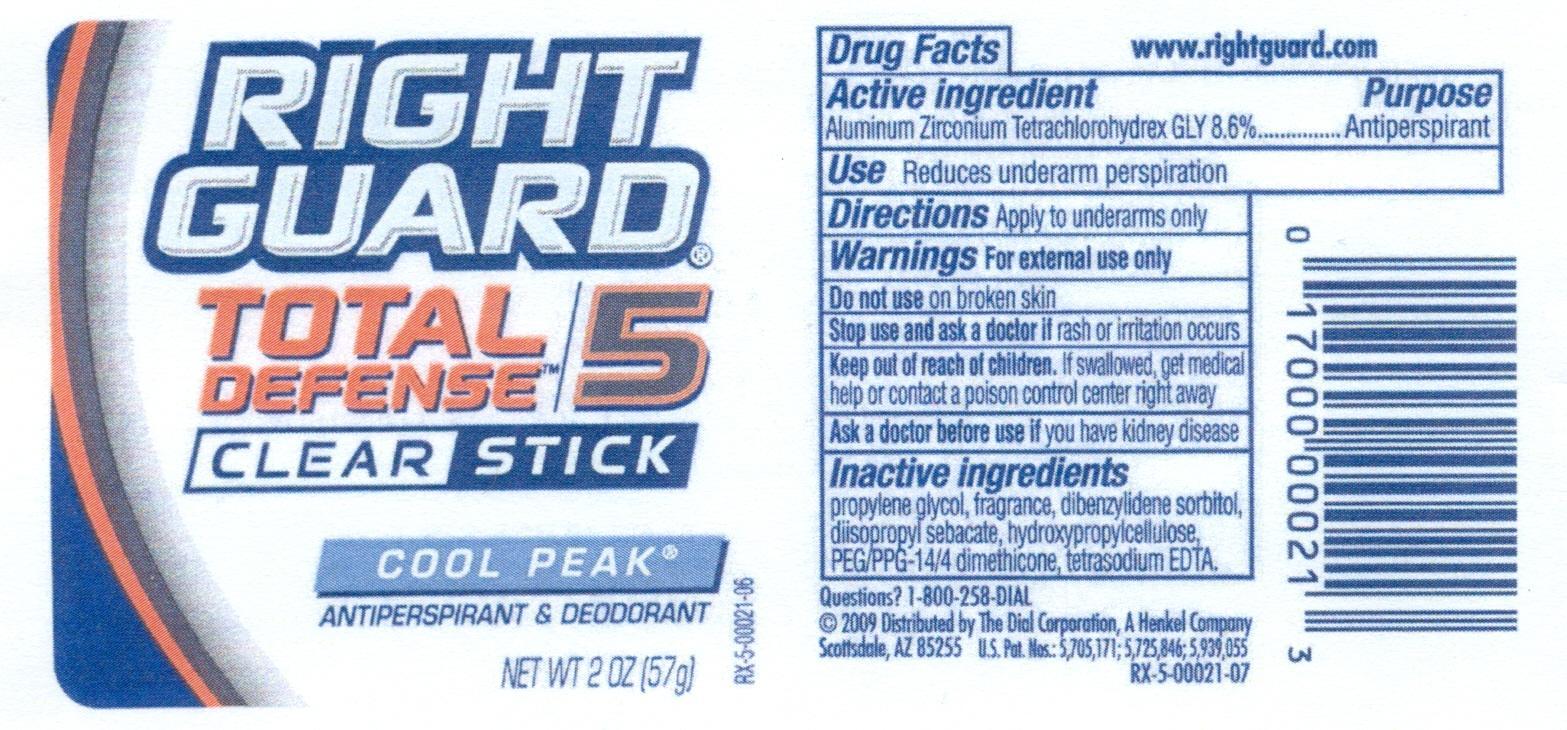 DRUG LABEL: Right Guard Total Defense Cool Peak
NDC: 54340-701 | Form: STICK
Manufacturer: The Dial Corporation
Category: otc | Type: HUMAN OTC DRUG LABEL
Date: 20120726

ACTIVE INGREDIENTS: ALUMINUM ZIRCONIUM TETRACHLOROHYDREX GLY 4.902 g/57 g
INACTIVE INGREDIENTS: PROPYLENE GLYCOL; DIISOPROPYL SEBACATE; HYDROXYPROPYL CELLULOSE; PEG/PPG-14/4 DIMETHICONE; DIBENZYLIDENE SORBITOL; EDETATE SODIUM

Right Guard Total Defense Clear Stick Cool Peak Antiperspirant/Deodorant

Active Ingredient: Aluminum Zirconium Tetrachlorohydrex Gly

Purpose: Antiperspirant

INDICATIONS AND USAGE

Use: Reduces underarm perspiration

Warnings: For external use only

Do not use on broken skin

Stop use and ask a doctor if rash or irritation occurs

Keep out of reach of children. If swallowed, get medial help or contact a poison control center right away.

Ask a doctor before use if you have kidney disease.

INACTIVE INGREDIENT

Propylene glycol, fragrance, dibenzylidene sorbitol, diisopropyl sebacate, hydroxypropylcellulose, PEG/PPG-14/4 dimethicone, tetrasodium EDTA

Questions: 1-800-258-DIAL

HOW SUPPLIED

2009 Distributed by The Dial Corporation, A Henkel Company, Scottsdale, AZ.85255. The distinctive design and elements of this package are proprietary and owned by the Dial Corporation, a Henkel Company.

DOSAGE AND ADMINISTRATION

Directions: Apply to underarms only.